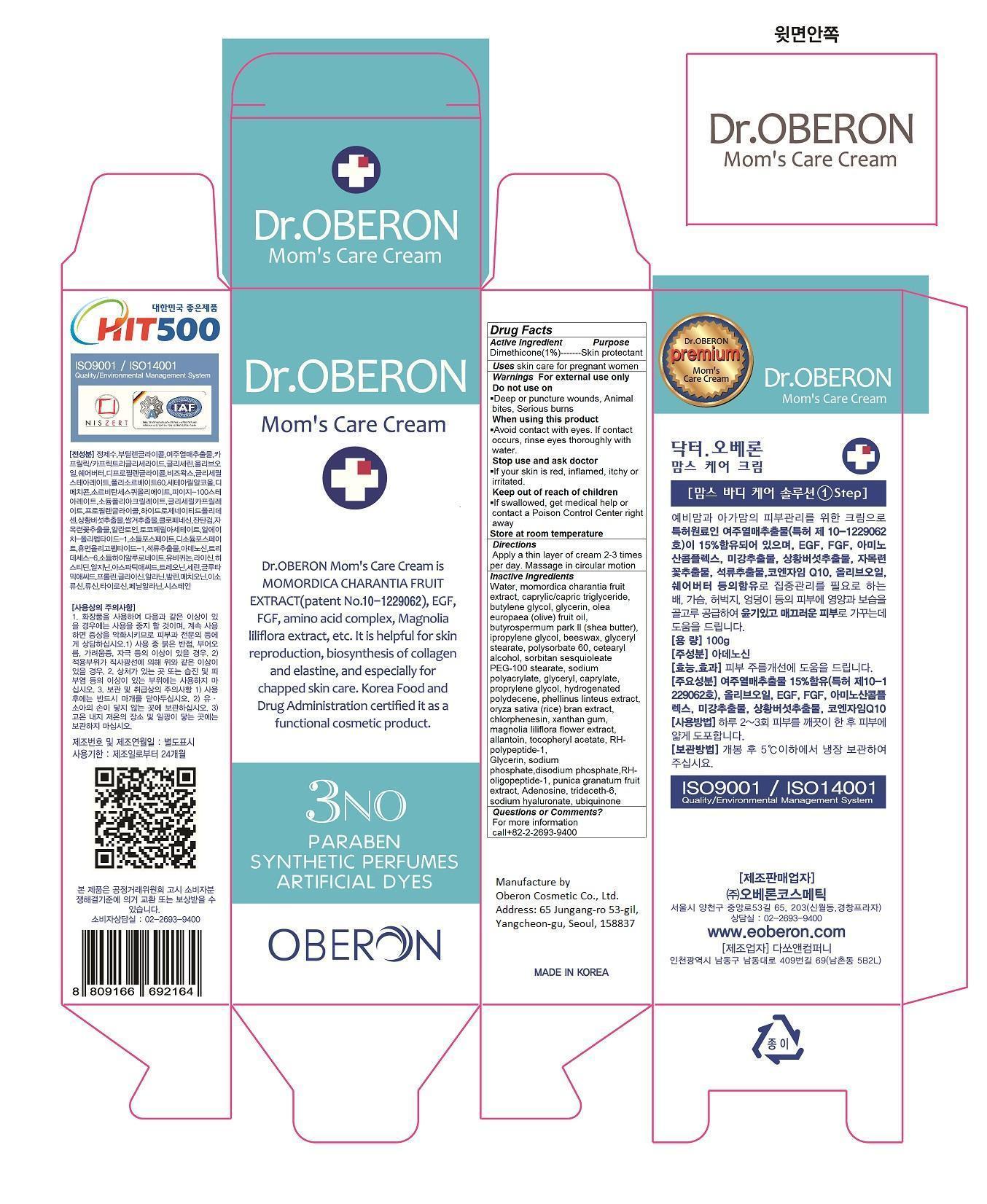 DRUG LABEL: Dr. Oberon Moms Care Cream
NDC: 52891-100 | Form: CREAM
Manufacturer: Oberon Cosmetic Co., Ltd.
Category: otc | Type: HUMAN OTC DRUG LABEL
Date: 20140529

ACTIVE INGREDIENTS: DIMETHICONE 1 g/100 g
INACTIVE INGREDIENTS: water; CAPRYLIC/CAPRIC/LAURIC TRIGLYCERIDE; MOMORDICA CHARANTIA FRUIT; butylene glycol; glycerin; OLEA EUROPAEA FRUIT VOLATILE OIL; SHEA BUTTER; dipropylene glycol; YELLOW WAX; GLYCERYL STEARATE SE; polysorbate 60; SORBITAN SESQUIOLEATE; PEG-100 stearate; SODIUM POLYACRYLATE (2500000 MW); glyceryl caprylate; HYDROGENATED POLYDECENE (550 MW); PHELLINUS LINTEUS WHOLE; ORYZA SATIVA WHOLE; chlorphenesin; xanthan gum; MAGNOLIA LILIIFLORA FLOWER; allantoin

Dr. Oberon Mom's Care Cream